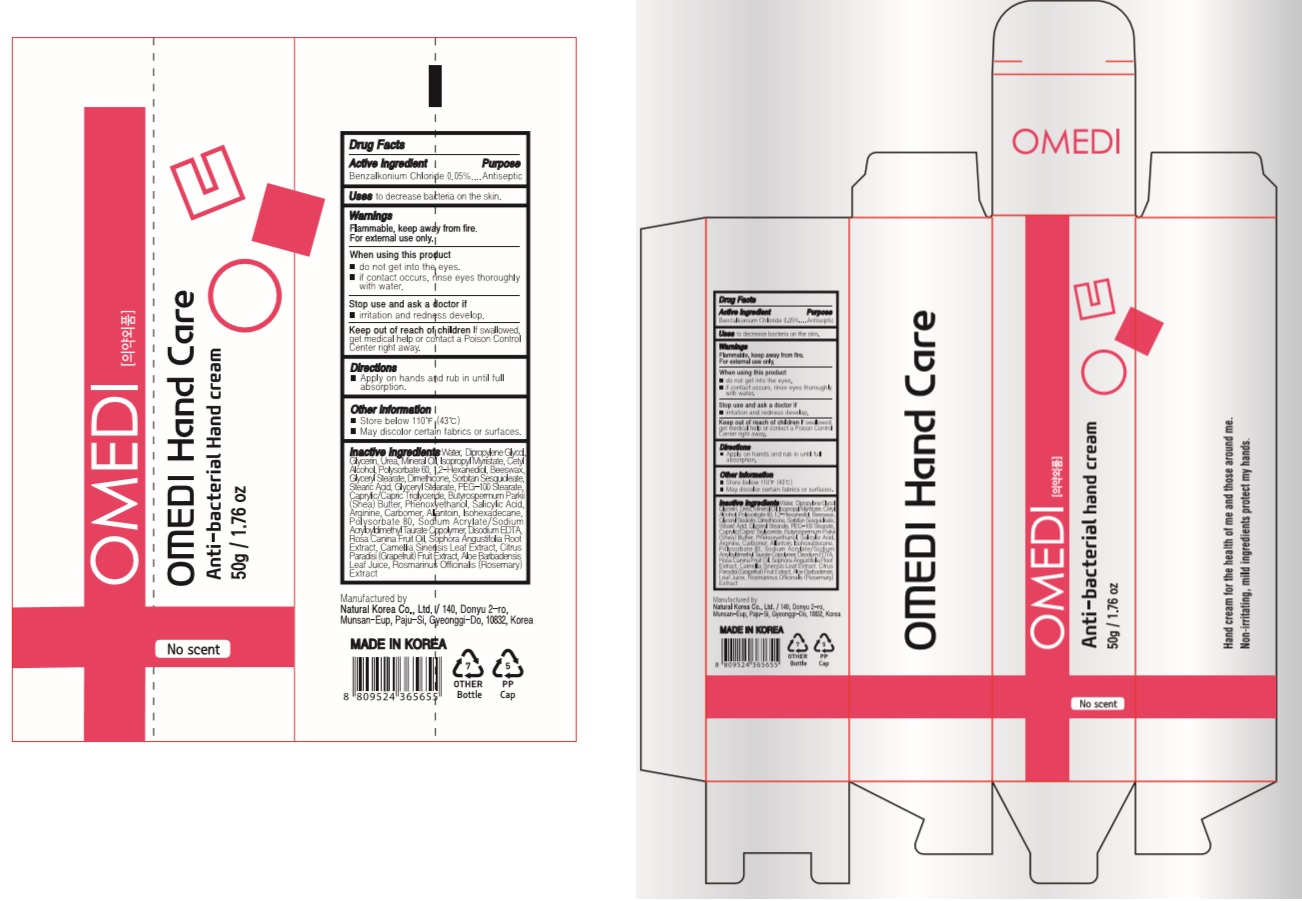 DRUG LABEL: OMEDI Anti-bacterial hand cream
NDC: 74646-3050 | Form: CREAM
Manufacturer: Natural Korea Co., Ltd.
Category: otc | Type: HUMAN OTC DRUG LABEL
Date: 20200601

ACTIVE INGREDIENTS: BENZALKONIUM CHLORIDE 0.025 g/50 g
INACTIVE INGREDIENTS: STEARIC ACID; PHENOXYETHANOL; SODIUM ACRYLATE/SODIUM ACRYLOYLDIMETHYLTAURATE COPOLYMER (4000000 MW); SOPHORA FLAVESCENS ROOT; DIMETHICONE; ALLANTOIN; ISOHEXADECANE; EDETATE DISODIUM; 1,2-HEXANEDIOL; WATER; DIPROPYLENE GLYCOL; GLYCERIN; UREA; YELLOW WAX; MINERAL OIL; ISOPROPYL MYRISTATE; CETYL ALCOHOL; POLYSORBATE 60; ALOE VERA LEAF; MEDIUM-CHAIN TRIGLYCERIDES; SHEA BUTTER; SALICYLIC ACID; ARGININE; CARBOMER HOMOPOLYMER, UNSPECIFIED TYPE; POLYSORBATE 80; ROSA CANINA FRUIT OIL; GREEN TEA LEAF; GRAPEFRUIT; ROSEMARY; PEG-100 STEARATE; SORBITAN SESQUIOLEATE; GLYCERYL MONOSTEARATE

OMEDI HAND CARE : OMEDI Anti-bacterial hand cream (No scent)
74646-3050-1 : TUBE
74646-3050-2 : TUBE+BOX